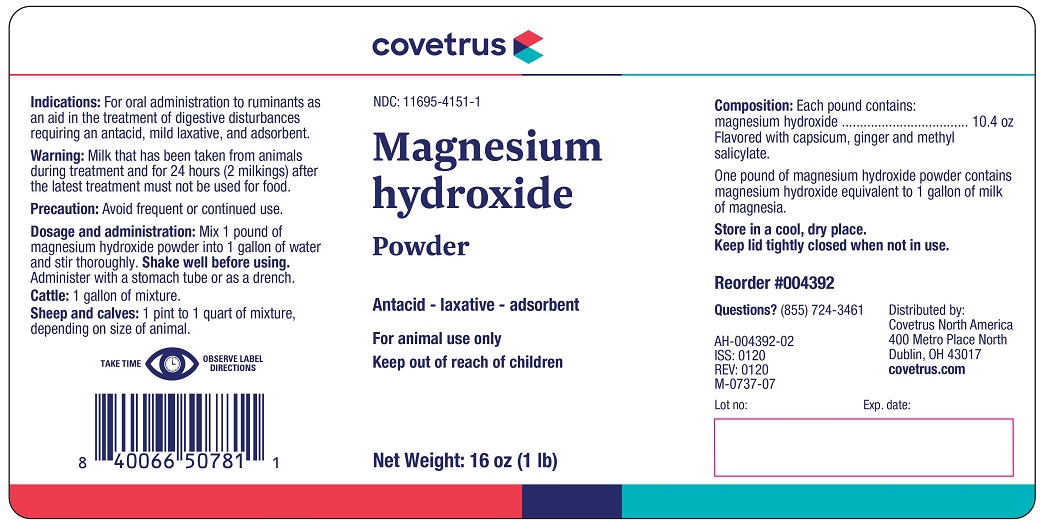 DRUG LABEL: MAGNALAX
NDC: 11695-4151 | Form: POWDER, FOR SOLUTION
Manufacturer: Covetrus North America
Category: animal | Type: OTC ANIMAL DRUG LABEL
Date: 20201106

ACTIVE INGREDIENTS: MAGNESIUM HYDROXIDE 293.7 g/454 g

MAGNALAX POWDER

INDICATIONS AND USAGE

Antacid - laxative - absorbent

For animal use only

Keep out of reach of children

INDICATIONS

For oral adminstration to ruminants as an aid in the treatment of digestive disturbances requiring an antacid, mild laxative and absorbent.

WARNINGS AND PRECAUTIONS

Warning: Milk that has been taken from animals during treatment and for 24 hours (2 milkings) after the latest treatment must not be used for food.

Precaution: Avoid frequent or continued use.

Dosage and administration: Mix 1 pound of magnesium hydroxide powder into 1 gallon of water and stir thoroughly. Shake well before using.Administer with a stomach tube or as a drench.

Cattle: 1 gallon of mixture

Sheep and calves: 1 pint to 1 quart of mixture, depending on the size of animal

TAKE TIME OBSERVE LABEL INSTRUCTIONS

COMPONENTS

Composition: Each pound contains:

magnesium hydroxide ................. 10.4 oz

Flavored with capsicum, ginger and methyl salicylate.

One pound of magnesium hydroxide powder contains magnesium hydroxide equivalent to 1 gallon of mik of magnesia

STORAGE AND HANDLING

Store in a cool, dry place.

Keep lid tightly closed when not in use.